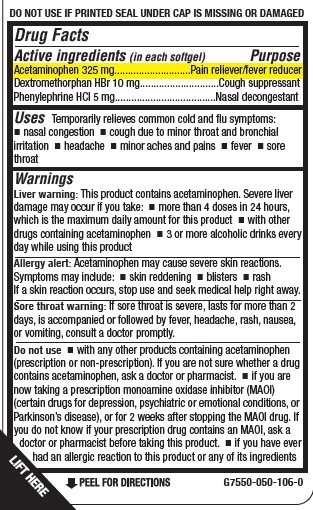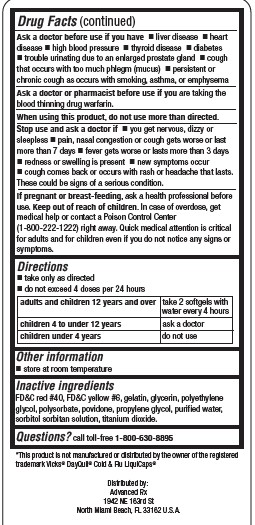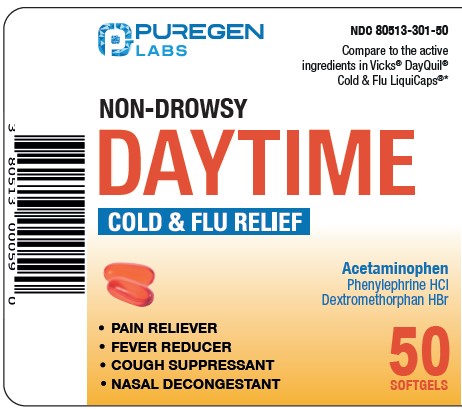 DRUG LABEL: DAYTIME COLD AND FLU RELIEF SOFTGELS

NDC: 80513-301 | Form: CAPSULE, GELATIN COATED
Manufacturer: Advanced Rx LLC
Category: otc | Type: HUMAN OTC DRUG LABEL
Date: 20240913

ACTIVE INGREDIENTS: DEXTROMETHORPHAN HYDROBROMIDE 10 mg/1 1; DIPHENHYDRAMINE HYDROCHLORIDE 5 mg/1 1; ACETAMINOPHEN 325 mg/1 1
INACTIVE INGREDIENTS: FD&C RED NO. 40; POLAWAX POLYSORBATE; FD&C YELLOW NO. 6; POVIDONE; TITANIUM DIOXIDE; GLYCERIN; GELATIN TYPE B BOVINE (160 BLOOM); POLYETHYLENE GLYCOL, UNSPECIFIED; WATER; SORBITOL SOLUTION; PROPYLENE GLYCOL

Advanced Rx - PUREGEN - NON-DROWSY DAYTIME COLD & FLU RELIEF (80513-301)

ACTIVE INGREDIENT (IN EACH SOFTGEL)

Acetaminophen 325 mg
Dextromethorphan HBr 10 mg
Phenylephrine HCl 5 mg

PURPOSE

Pain reliever/fever reducer
Cough suppressant
Nasal decongestant

USES

Temporarily relieves common cold and flu symptoms:

- nasal congestion
- cough due to minor throat and bronchial irritation
- headache
- minor aches and pains
- fever
- sore throat

WARNINGS

Liver warning: This product contains acetaminophen. Severe liver damage may occur if you take:

- more than 4 doses in 24 hours, which is the maximum daily amount for this product
- with other drugs containing acetaminophen
- 3 or more alcoholic drinks every day while using this product

Allergy alert: Acetaminophen may cause severe skin reactions. Symptoms may include:

- skin reddening
- blisters
- rash

If a skin reaction occurs, stop use and seek medical help right away.

Sore throat warning: If sore throat is severe, lasts for more than 2 days, is accompanied or followed by fever, headache, rash, nausea, or vomiting, consult a doctor promptly.

Do not use

- with any other products containing acetaminophen (prescription or non-prescription). If you are not sure whether a drug

contains acetaminophen, ask a doctor or pharmacist.

- if you are now taking a prescription monoamine oxidase inhibitor (MAOI) (certain drugs for depression, psychiatric or emotional conditions, or Parkinson’s disease), or for 2 weeks after stopping the MAOI drug. If you do not know if your prescription drug contains an MAOI, ask a doctor or pharmacist before taking this product.
- if you have ever had an allergic reaction to this product or any of its ingredients

Ask a doctor before use if you have

- liver disease
- heart disease
- high blood pressure
- thyroid disease
- diabetes
- trouble urinating due to an enlarged prostate gland
- cough that occurs with too much phlegm (mucus)
- persistent or chronic cough as occurs with smoking, asthma, or emphysema

Ask a doctor or pharmacist before use if you are taking the blood thinning drug warfarin.

When using this product, do not use more than directed.

Stop use and ask a doctor if

- you get nervous, dizzy or sleepless
- pain, nasal congestion or cough gets worse or last more than 7 days
- fever gets worse or lasts more than 3 days
- redness or swelling is present  new symptoms occur
- cough comes back or occurs with rash or headache that lasts.

These could be signs of a serious condition.

If pregnant or breast-feeding, ask a health professional before use.

Keep out of reach of children. In case of overdose, get medical help or contact a Poison Control Center (1-800-222-1222) right away. Quick medical attention is critical for adults and for children even if you do not notice any signs or symptoms.

DIRECTIONS

- take only as directed
- do not exceed 4 doses per 24 hours

adults and children 12 years and over | take 2 softgels with water every 4 hours
children 4 to under 12 years | ask a doctor
children under 4 years | do not use

OTHER INFORMATION

- store at room temperature

INACTIVE INGREDIENTS

FD&C red #40, FD&C yellow #6, gelatin, glycerin, polyethylene glycol, polysorbate, povidone, propylene glycol, purified water,
sorbitol sorbitan solution, titanium dioxide.

QUESTIONS?

call toll-free 1-800-630-8895